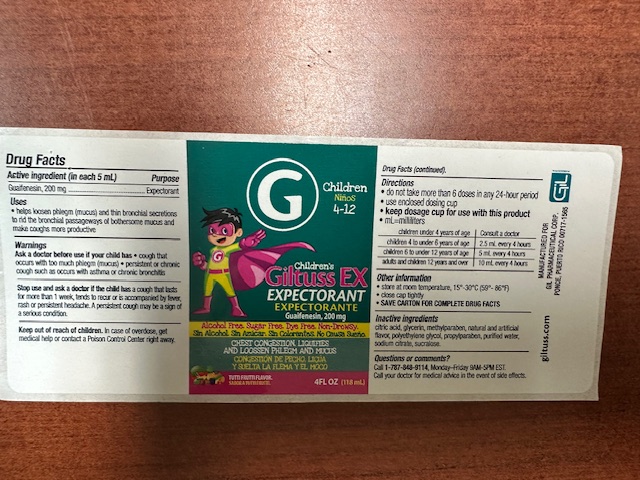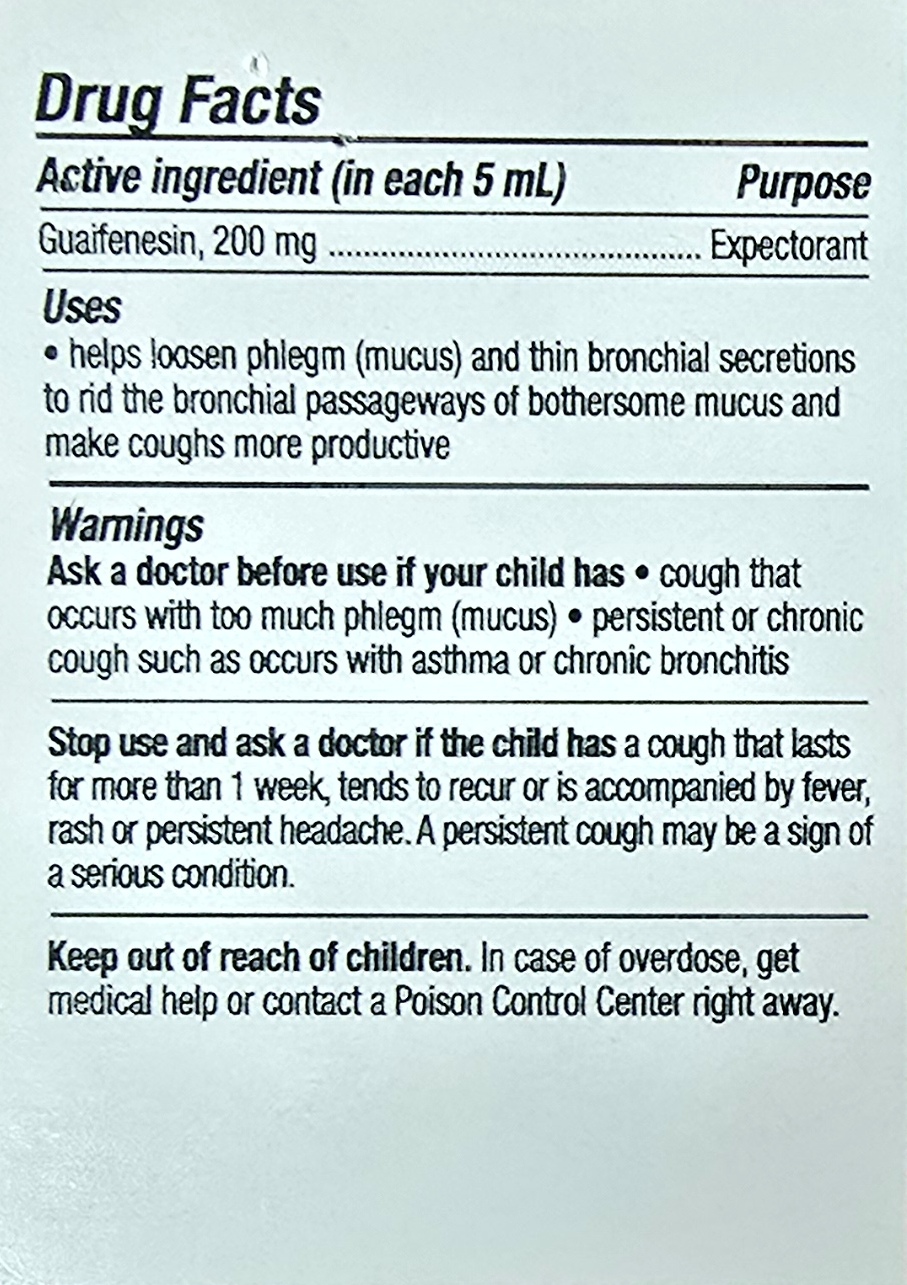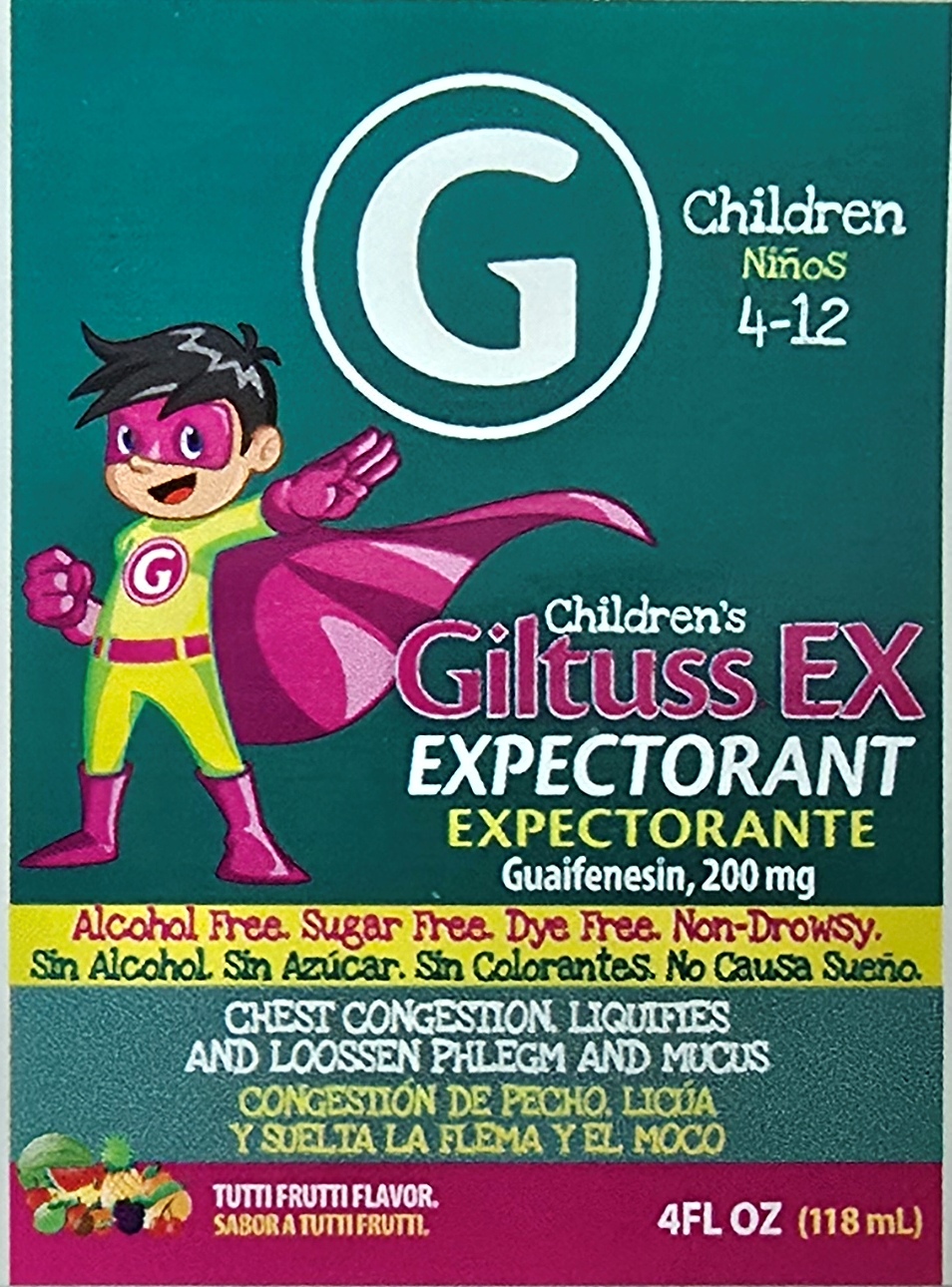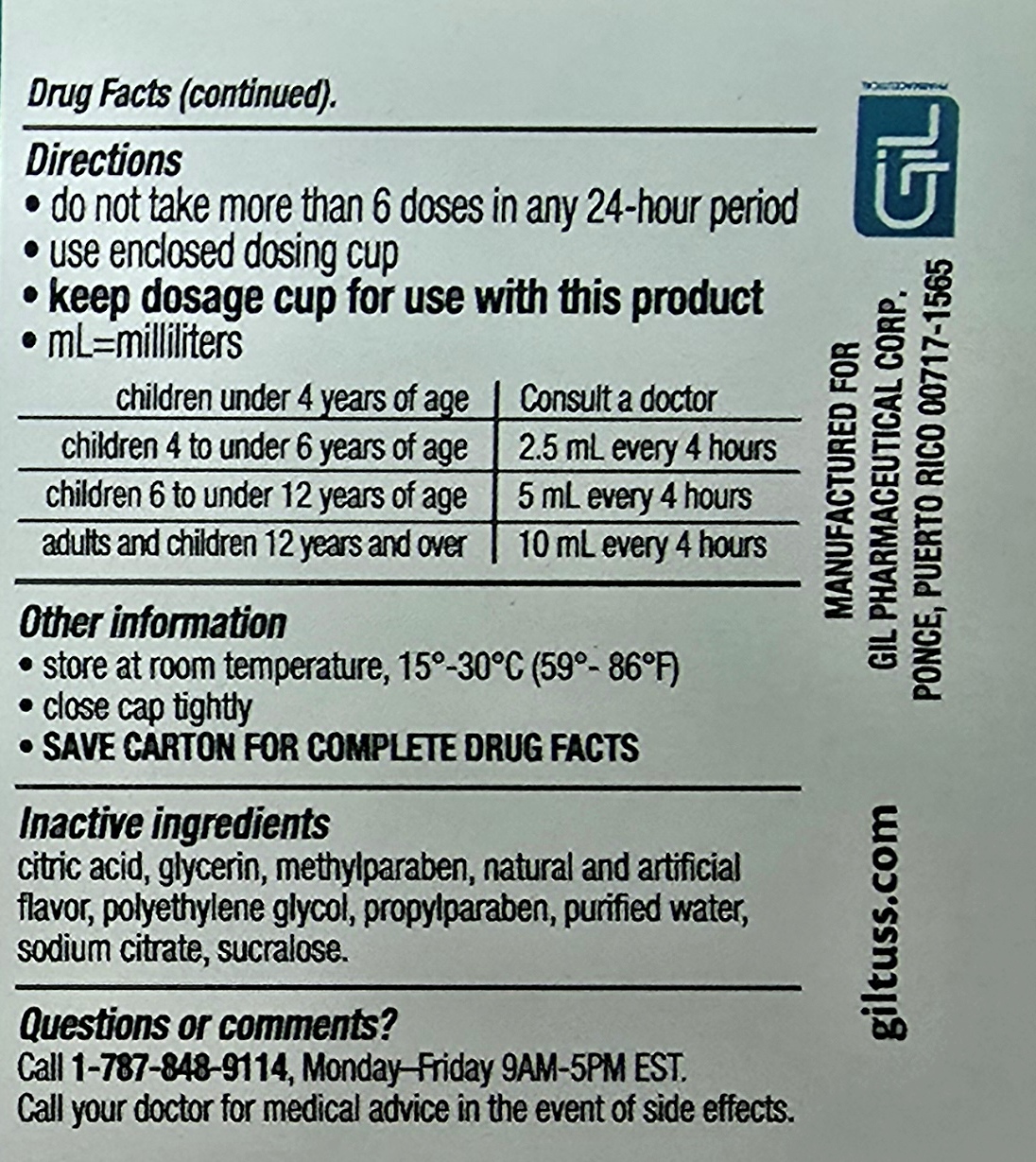 DRUG LABEL: Childrens Giltuss EX Expectorant
NDC: 65852-016 | Form: SOLUTION
Manufacturer: Dextrum Laboratories Inc.
Category: otc | Type: HUMAN OTC DRUG LABEL
Date: 20250924

ACTIVE INGREDIENTS: GUAIFENESIN 200 mg/5 mL
INACTIVE INGREDIENTS: METHYLPARABEN; POLYETHYLENE GLYCOL, UNSPECIFIED; GLYCERIN; PROPYLPARABEN; SUCRALOSE; WATER; CITRIC ACID; SODIUM CITRATE

Children's Giltuss Ex Expectorant

Active Ingredients

Active ingredients (in each 5 ml) Purpose

Guaifenesin, 200 mg ----------------------------------------Expectorant

Directions

Do not take more than 6 doses in any 24 hours period

use enclosed dosing cup

Keep dosage cup for use with this product

ml= mililiters

children under 4 years of age Consult a doctor

children 4 to under 6 years of age 2.5 ml every 4 hours

children 6 to under 12 years of age 5 ml every 4 hours

Adults and children 12 years & over 10 ml every 4 hours

Other Information

Store at room temperature 15-30 °C (59° -86 ° F)
Close cap tightly
SAVE CARTON FOR COMPLETE DRUG FACTS

Inactive Ingredients

Citric Acid, glycerin, methylparaben, natural and artificial flavor, polyethylene glycol, propylparaben, purified water, sodium citrate, sucralose

Questions or comments

Call 1-787-848-9114, Monday-Friday 9AM – 5PM EST

Call your doctor for medical advice in the event of side effects.

indication for use section

indication an user section

Do not take more than 6 doses in any 24 hours period

use enclosed dosing cup

Keep dosage cup for use with this product

ml= mililiters

children under 4 years of age Consult a doctor

children 4 to under 6 years of age 2.5 ml every 4 hours

children 6 to under 12 years of age 5 ml every 4 hours

Adults and children 12 years & over 10 ml every 4 hours

PACKAGE LABEL

Children 4 -12

Children's Giltuss EX

Expectorant

Guaifenesin, 200 mg

Alcohol free, Sugar free, Dye free, Non-Drowsy

Chest congestion liquifies and loosen phlegm and mucus

Tutti Frutti flavor

4 floz 118 ml